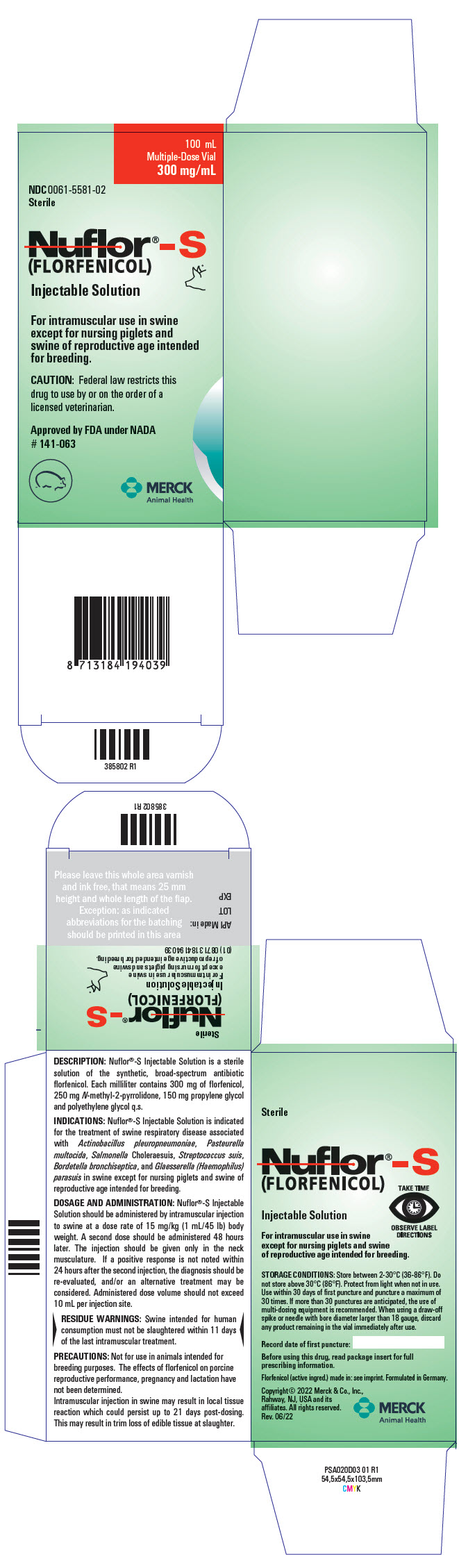 DRUG LABEL: Nuflor-S
NDC: 0061-5581 | Form: INJECTION
Manufacturer: Merck Sharp & Dohme Corp.
Category: animal | Type: PRESCRIPTION ANIMAL DRUG LABEL
Date: 20250915

ACTIVE INGREDIENTS: FLORFENICOL 300 mg/1 mL

Nuflor®-S
(FLORFENICOL)
Injectable Solution
300 mg/mL

PRODUCT
INFORMATION

For intramuscular use in swine except for nursing piglets and swine of reproductive age intended for breeding.

CAUTION: Federal law restricts this drug to use by or on the order of a licensed veterinarian.

DESCRIPTION

DESCRIPTION: Nuflor®-S Injectable Solution is a sterile solution of the synthetic, broad-spectrum antibiotic florfenicol. Each milliliter of sterile Nuflor®-S Injectable Solution contains 300 mg of florfenicol, 250 mg N-methyl-2-pyrrolidone (NMP), 150 mg propylene glycol and polyethylene glycol q.s.

VETERINARY INDICATIONS

INDICATIONS: Nuflor®-S Injectable Solution is indicated for treatment of swine respiratory disease associated with Actinobacillus pleuropneumoniae, Pasteurella multocida, Salmonella Choleraesuis, Streptococcus suis, Bordetella bronchiseptica, and Glaesserella (Haemophilus) parasuis in swine except for nursing piglets and swine of reproductive age intended for breeding.

DOSAGE AND ADMINISTRATION: Nuflor®-S Injectable Solution should be administered by intramuscular injection to swine at a dose rate of 15 mg/kg (1 mL/45 lb) body weight. A second dose should be administered 48 hours later. The injection should be given only in the neck musculature. If a positive response is not noted within 24 hours after the second injection, the diagnosis should be re-evaluated, and/or an alternative treatment may be considered. Administered dose volume should not exceed 10 mL per injection site.

Nuflor®-S DOSAGE GUIDE FOR SWINE
ANIMAL WEIGHT (lbs) | IM Nuflor®-S DOSAGE (1 mL/ 45 lb Body Weight) (mL)
22 | 0.5
45 | 1
90 | 2
135 | 3
180 | 4
225 | 5
270 | 6

WARNINGS

WARNINGS: NOT FOR HUMAN USE. KEEP OUT OF REACH OF CHILDREN. This product contains materials that can be irritating to skin and eyes. Avoid direct contact with skin, eyes and clothing. In case of accidental eye exposure, flush with water for 15 minutes. In case of accidental skin exposure, wash with soap and water. Remove contaminated clothing. Consult a physician if irritation persists. Accidental injection of this product may cause local irritation. Consult a physician immediately. Reproductive and developmental toxicities have been reported in laboratory animals following high, repeated exposures to NMP. Pregnant women should wear gloves and exercise caution or avoid handling this product. The Safety Data Sheet (SDS) contains more detailed occupational safety information.

For customer service, adverse effects reporting and/or a copy of the SDS, call 1-800-211-3573. For additional information about adverse drug experience reporting for animal drugs, contact FDA at 1-888-FDA-VETS or online at www.fda.gov/reportanimalae.

PRECAUTIONS

PRECAUTIONS: Not for use in animals intended for breeding purposes. The effects of florfenicol on porcine reproductive performance, pregnancy and lactation have not been determined.

Intramuscular injection in swine may result in local tissue reaction which could persist up to 21 days post-dosing. This may result in trim loss of edible tissue at slaughter.

RESIDUE WARNING

RESIDUE WARNINGS: Swine intended for human consumption must not be slaughtered within 11 days of the last intramuscular treatment.

ADVERSE REACTIONS

ADVERSE REACTIONS: Perianal inflammation, rectal eversion, rectal prolapse and diarrhea may occur transiently following treatment. Decreased feed and water consumption may occur if the labeled dosage regimen is exceeded.

CLINICAL PHARMACOLOGY

CLINICAL PHARMACOLOGY: The pharmacokinetic disposition of florfenicol was evaluated in 20 pigs following a single IM injection of Nuflor®-S at the labeled dose of 15 mg/kg BW. The mean ± standard deviation maximum plasma concentration (Cmax) and the time to reach Cmax (Tmax) of florfenicol were 3.42 ± 0.82 μg/mL and 4.70 ± 2.15 hours, respectively. The mean ± standard deviation area under the drug concentration-time curve between times 0 and the last quantifiable concentration (AUC0-LOQ) and the terminal half-life (T1/2) of florfenicol were 70.34 ± 23.78 μg*hours/mL and 11.21 ± 3.73 hours, respectively.

MICROBIOLOGY

MICROBIOLOGY: Florfenicol is a synthetic, broad-spectrum antibiotic active against many Gram-negative and Gram-positive bacteria isolated from domestic animals. It acts by binding to the 50S ribosomal subunit and inhibiting bacterial protein synthesis. Florfenicol is generally considered a bacteriostatic drug, but exhibits bactericidal activity against certain bacterial species.

In vitro activity of florfenicol has been demonstrated against commonly isolated pathogens associated with swine respiratory disease. Isolates tested were obtained from pre-treatment lung samples from representative non-enrolled pigs at each study site and post-treatment lung samples from pigs in the florfenicol-treated and saline-treated groups that died or were euthanized during the study, or were classified as treatment failures at the end of the study. The minimum inhibitory concentrations (MICs) of florfenicol for swine respiratory pathogens from clinical studies were determined using dilution methods. These susceptibility test methods were adequately controlled with the inclusion and acceptable performance of appropriate reference strains. The results are presented in Table 1.

Table 1. Florfenicol minimum inhibitory concentration (MIC) values [The correlation between in vitro susceptibility data and the clinical effectiveness of florfenicol is unknown.] for indicated target pathogens isolated from a multi-site field study evaluating swine respiratory disease in the U.S. in 2001.
Indicated pathogens | Number of Isolates | MIC50 [The lowest MIC to encompass 50% and 90% of the most susceptible isolates, respectively.] (μg/mL) | MIC90 (μg/mL) | MIC Range (μg/mL)
Actinobacillus pleuropneumoniae | 100 | 0.25 | 0.5 | 0.25-1
Pasteurella multocida | 107 | 0.5 | 0.5 | 0.25-0.5
Bordetella bronchiseptica | 49 | 2 | 2 | 0.5-4
Glaesserella parasuis | 36 | 0.5 | 0.5 | ≤0.12-1.0
Streptococcus suis | 62 | 2 | 2 | 1-2
Salmonella Choleraesuis | 36 | 4 | 4 | 2-4

EFFECTIVENESS: In a multi-site natural infection field study, a total of 620 growing pigs with clinical signs of SRD (rectal temperature of ≥ 104.5°F, and a depression score (on a scale of 0 [absent] to 3 [severe]) of ≥ 2, and a dyspnea score (on a scale of 0 [absent] to 3 [severe]) of ≥ 2) were treated with either florfenicol (15 mg/kg BW IM given on Days 0 and 2) or an equivalent volume of saline. Treatment success (rectal temperature of < 104°F, and a depression score of 0 or 1, and a dyspnea score of 0 or 1) was evaluated on Day 6. The treatment success rate was statistically significantly different (p < 0.0001) and higher in the florfenicol-treated group (72%) than in the saline-treated control group (33.1%).

ANIMAL SAFETY: A safety study was conducted in 40 healthy crossbred growing pigs. Pigs were administered florfenicol by IM injection in the neck at 1X, 3X, or 5X the labeled dose (15, 45, or 75 mg/kg BW, respectively) for 3X the labeled duration of treatment (6 injections at 48-hour intervals), or 10X the labeled dose (150 mg/kg BW) administered as two injections 48 hours apart. Test article-related diarrhea (moderate), anal swelling/erythema (mild to moderate), and injection site swelling (mild to moderate) were seen in all florfenicol-treated groups after dosing, most frequently in the 3X and 5X groups. Although these findings were considered clinically relevant, the incidence and severity in the 1X group was considered within acceptable limits. Test article-related decreases in feed and water consumption and an associated decrease in body weight were seen in the 3X and 5X groups. Test article-related changes in some serum chemistry parameters and decreased numbers of white blood cells were seen in the 3X, 5X, and/or 10X groups; the changes were generally minimal and not considered clinically significant. Most changes in drug-related, in-life parameters did not become apparent until after dosing was extended beyond the labeled duration of two injections, 48 hours apart.

Injection site irritation was evaluated in a safety study using 20 healthy crossbred growing pigs administered florfenicol at 15 mg/kg BW IM in the neck as two injections 48 hours apart. Mild injection site swelling was seen in up to approximately 32% of the pigs by 4 days post-injection and was resolved by 16 days post-injection. Gross and histopathologic evaluation showed that injection site discoloration and inflammation was present at 7 and 14 days post-injection, and absent at 21, 28, and 42 days post-injection.

STORAGE AND HANDLING

STORAGE CONDITIONS: Store between 2-30°C (36-86°F). Do not store above 30°C (86°F). Protect from light when not in use. Use within 30 days of first puncture and puncture a maximum of 30 times. If more than 30 punctures are anticipated, the use of multi-dosing equipment is recommended. When using a draw-off spike or needle with bore diameter larger than 18 gauge, discard any product remaining in the vial immediately after use.

HOW SUPPLIED

HOW SUPPLIED: Nuflor®-S (florfenicol) Injectable Solution is packaged in 100 mL glass sterile multiple dose vials.

Approved by FDA under NADA # 141-063
Formulated in Germany.
Copyright© 2022 Merck & Co., Inc., Rahway, NJ, USA
and its affiliates. All rights reserved.
Rev. 06/22

394544 R1

PRINCIPAL DISPLAY PANEL - 100 mL Vial Carton

100 mL
Multiple-Dose Vial
300 mg/mL

NDC 0061-5581-02
Sterile

Nuflor®-S
(FLORFENICOL)
Injectable Solution

For intramuscular use in swine
except for nursing piglets and
swine of reproductive age intended
for breeding.

CAUTION: Federal law restricts this
drug to use by or on the order of a
licensed veterinarian.

Approved by FDA under NADA
# 141-063

MERCK
Animal Health